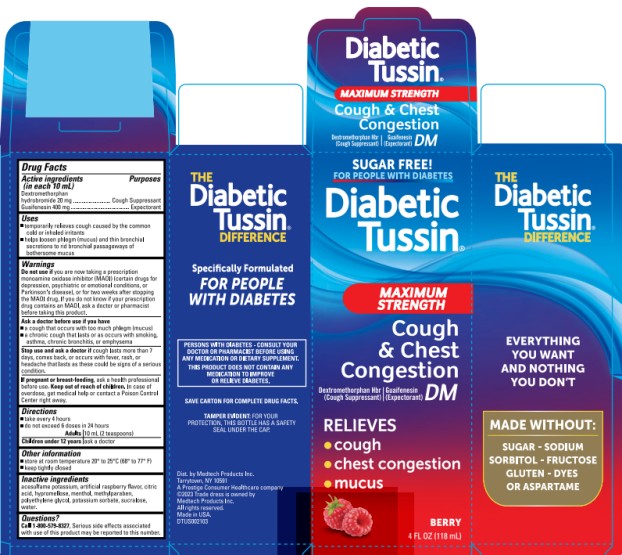 DRUG LABEL: Diabetic Tussin DM Maximum Strength
NDC: 61787-515 | Form: LIQUID
Manufacturer: MEDTECH PRODUCTS INC
Category: otc | Type: HUMAN OTC DRUG LABEL
Date: 20250808

ACTIVE INGREDIENTS: DEXTROMETHORPHAN HYDROBROMIDE 20 mg/10 mL; GUAIFENESIN 400 mg/10 mL
INACTIVE INGREDIENTS: ACESULFAME POTASSIUM; HYPROMELLOSE, UNSPECIFIED; MENTHOL, UNSPECIFIED FORM; METHYLPARABEN; POLYETHYLENE GLYCOL, UNSPECIFIED; POTASSIUM SORBATE; RASPBERRY; SUCRALOSE; WATER; ANHYDROUS CITRIC ACID

DiabeticTussin DM Max Strength 61787-515

Drug Facts

Active ingredients (in each 10 mL)

Dextromethorphan hydrobromide 20 mg

Guaifenesin 400 mg

Purposes

Cough Suppressant

Expectorant

Uses

- temporarily relieves cough caused by the common cold or inhaled irritants.
- helps loosen phlegm (mucus) and thin bronchial secretions to rid bronchial passageways of bothersome mucus.

Warnings

Do not use

if you are now taking a prescription monoamine oxidase inhibitor (MAOI) (certain drugs for depression, psychiatric or emotional conditions, or Parkinson's disease), or for two weeks after stopping the MAOI drug. If you do not know if your prescription drug contains an MAOI, ask a doctor or pharmacist before taking this product.

Ask a doctor before use if you have

- a cough that occurs with too much phlegm (mucus)
- a chronic cough that lasts or as occurs with smoking, asthma, chronic bronchitis, or emphysema

Stop use and ask a doctor if

- cough lasts more than 7 days, comes back, or occurs with fever, rash, or headache that lasts as these could be signs of a serious condition.

If pregnant or breast-feeding,

ask a health professional before use.

Keep out of reach of children.

In case of overdose, get medical help or contact a Poison Control Center right away.

Directions

- take every 4 hours
- do not exceed 6 doses in 24 hours

Adults | 10 mL (2 teaspoons)
Children under 12 years | ask a doctor

Other information

- store at room temperature 20-25ºC (68-77ºF)
- keep tightly closed

Inactive ingredients

acesulfame potassium, artificial raspberry flavor, citric acid, hypromellose, menthol, methylparaben, polyethylene glycol, potassium sorbate, sucralose, water.

Questions

Call 1-800-579-8327, serious side effects associated with use of this product may be reported to this number.

Package Principal Display Panel

Diabetic Tussin®

MAXIMUM STRENGTH

COUGH & CHEST CONGESTION

DM

Dextromethorphan HBr (Cough Suppressant)

Guaifenesin (Expectorant)

4 FL OZ (118 mL)